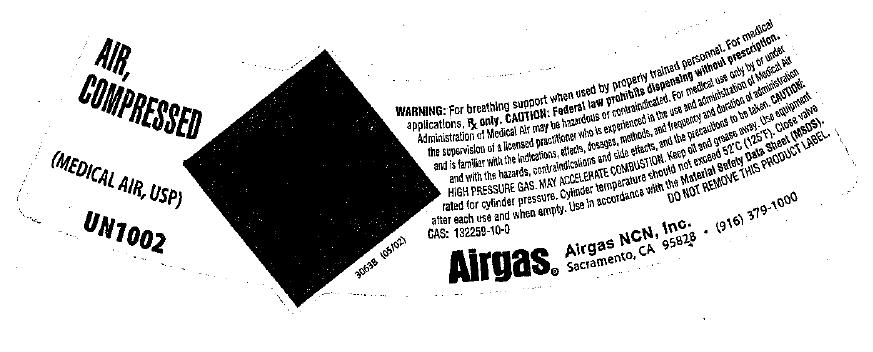 DRUG LABEL: Air
NDC: 58789-005 | Form: GAS
Manufacturer: Airgas Northern California and Nevada, Inc.
Category: prescription | Type: HUMAN PRESCRIPTION DRUG LABEL
Date: 20100430

ACTIVE INGREDIENTS: Air 1000 mL/1 L

air

PACKAGE LABEL

AIR, COMPRESSED (MEDICAL AIR, USP) UN 1002
WARNING: For breathing support when used by properly trained personnel. For medical applications. Rx only . CAUTION: Federal law prohibits dispensing without prescription. Administration of Medical Air may be hazardous or contraindicated. For medical use only by or under the supervision of a licensed practitioner who is experienced in the use and administration of Medical Air and is familiar with the indications, effects, dosages, methods, and frequency and duration of administration and with the hazards, contraindications and side effects, and the precautions to be taken. CAUTION: HIGH PRESSURE GAS. MAY ACCELERATE COMBUSTION. Keep oil and grease away. Use equipment rated for cylinder pressure. Cylinder temperature should not exceed 52C (125F). Close valve after each use and when empty. Use in accordance with the Material Safety Data Sheets (MSDS). DO NOT REMOVE THIS PRODUCT LABEL. CAS: 132259-10-0
Airgas Airgas NCN, Inc. Sacramento, CA 95828 * (916) 379-1000
30638 (05/02)